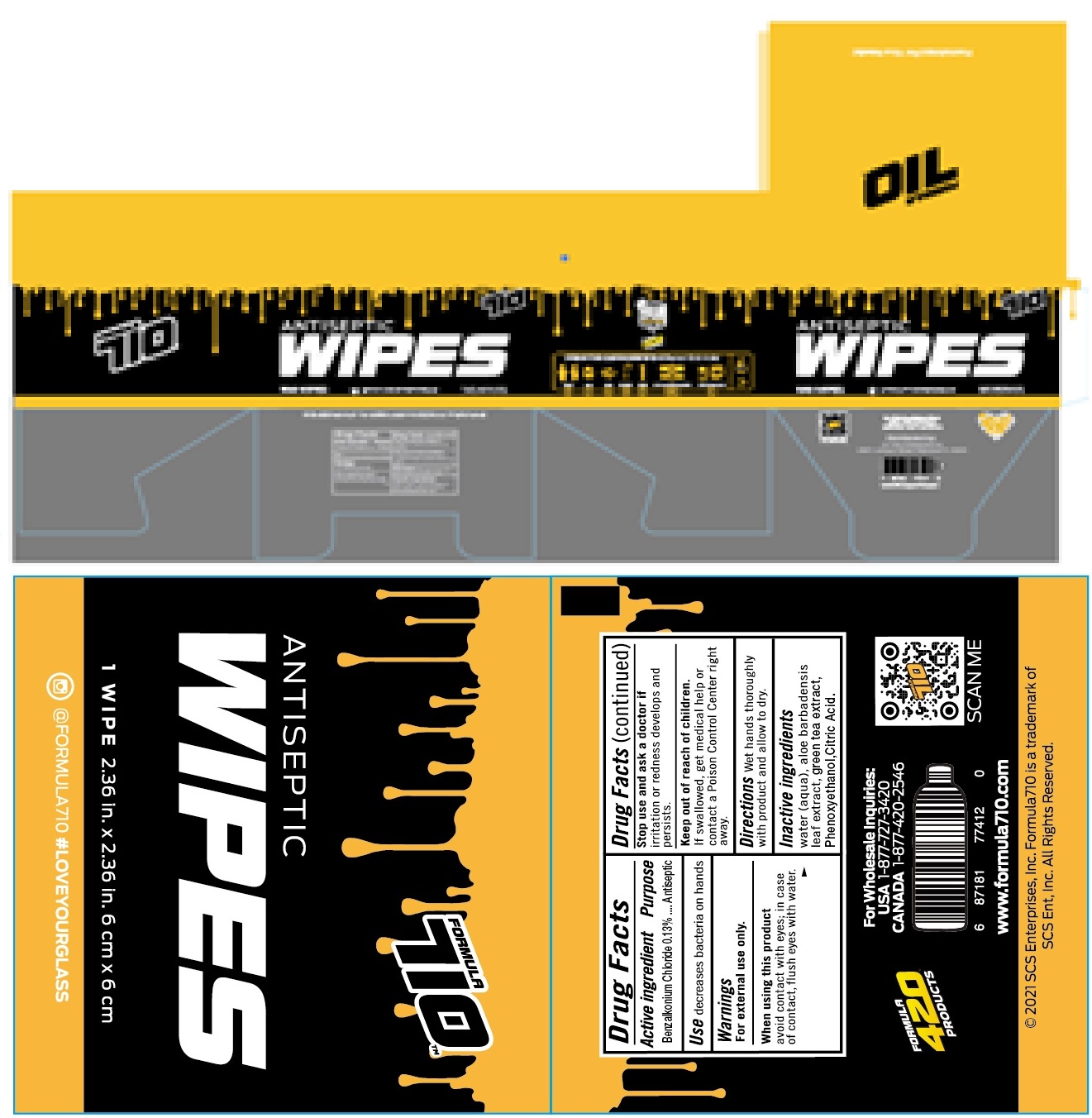 DRUG LABEL: Antiseptic Wipes
NDC: 77435-221 | Form: CLOTH
Manufacturer: HAINING LILY CLEANING PRODUCTS CO., LTD
Category: otc | Type: HUMAN OTC DRUG LABEL
Date: 20211030

ACTIVE INGREDIENTS: BENZALKONIUM CHLORIDE 0.13 g/100 g
INACTIVE INGREDIENTS: WATER; GREEN TEA LEAF; PHENOXYETHANOL; CITRIC ACID MONOHYDRATE

Antiseptic wipes

Active Ingredient

BENZALKONIUM CHLORIDE .......... 0.13%

Purpose

Antiseptic

USE

decrease bacteria on hands

Warning

- For external use only.
- When using this product, avoid contact with eyes; in case of contact, flush eyes with water.

- Stop use and ask a doctor, if irritaion or redness develops and persists.

KEEP OUT OF REACH OF CHILDREN

●If swallowed, get medical help or contact a Poison Contrl Center right away.

Directions

Wet hands thoroughluy with produt and allow to dry.

Inactive ingredients

water (aqua), aloe barbadensis leaf extract, green tea exract, phenoxyethanol, citric acid.